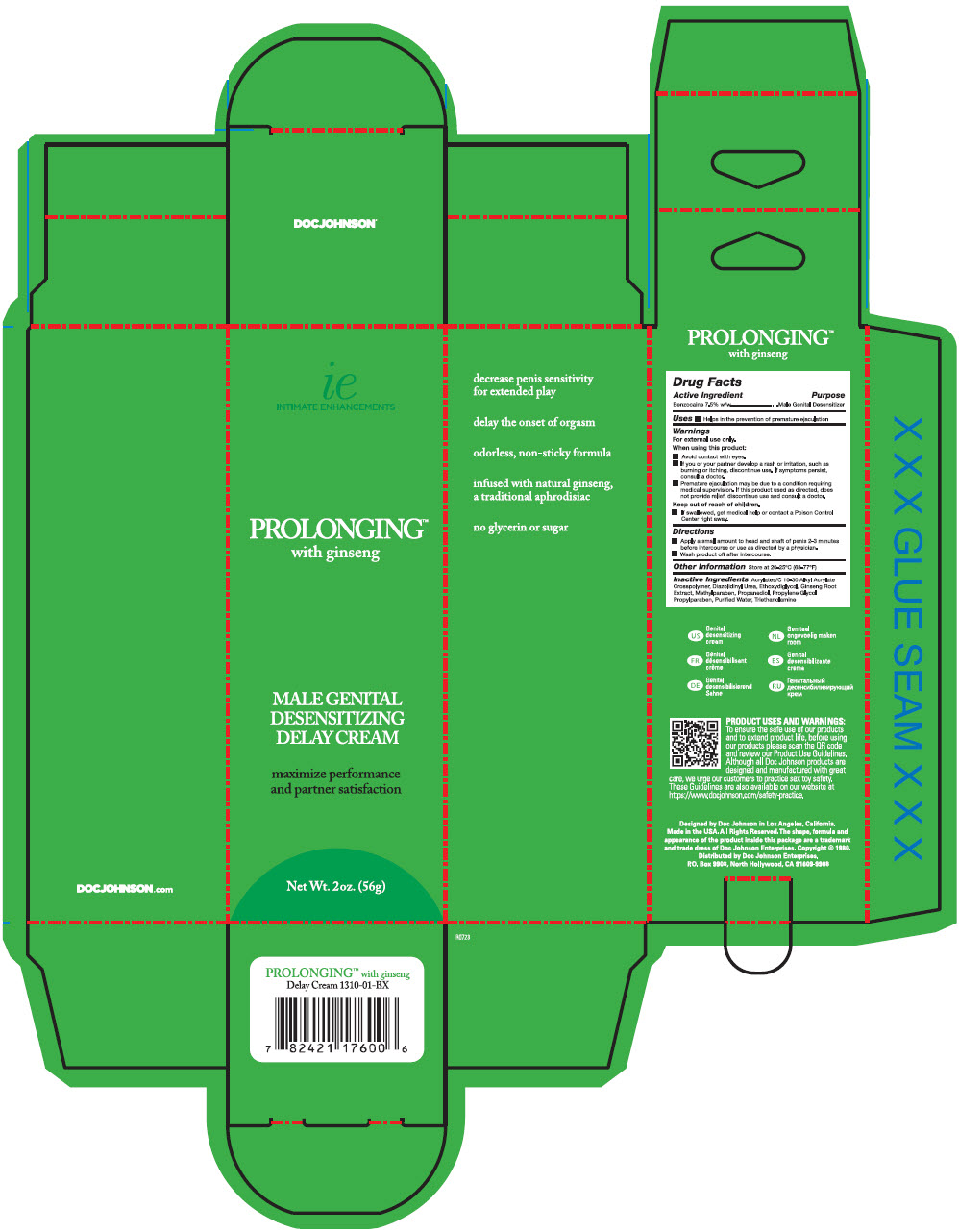 DRUG LABEL: Doc Johnson Prolonging Ginseng
NDC: 69503-003 | Form: CREAM
Manufacturer: Health Devices Corporation
Category: otc | Type: HUMAN OTC DRUG LABEL
Date: 20230814

ACTIVE INGREDIENTS: BENZOCAINE 7.5 g/100 g
INACTIVE INGREDIENTS: CARBOMER COPOLYMER TYPE B (ALLYL PENTAERYTHRITOL CROSSLINKED) 0.3 g/100 g; DIAZOLIDINYL UREA 0.3 g/100 g; DIETHYLENE GLYCOL MONOETHYL ETHER 15 g/100 g; METHYLPARABEN 0.11 g/100 g; ASIAN GINSENG 0.1 g/100 g; PROPANEDIOL 10 g/100 g; PROPYLENE GLYCOL 0.56 g/100 g; PROPYLPARABEN 0.03 g/100 g; WATER 65.8 g/100 g; TROLAMINE 0.3 g/100 g

Doc Johnson Prolonging™ Ginseng

Drug Facts

Active Ingredient

Benzocaine 7.5% w/w

Purpose

Male Genital Desensitizer

Use

- Helps in the prevention of premature ejaculation.

Warnings

For external use only

When using this product

- Avoid contact with eyes
- If you or your partner develop a rash or irritation, such as burning or itching, discontinue use. If symptoms persist, consult a doctor.
- Premature ejaculation may be due to a condition requiring medical supervision. If this product used as directed, does not provide relief, discontinue use and consult a doctor.

Keep out of reach of children. If swallowed, get medical help or contact a Poison Control Center right away.

Directions

- Apply a small amount to head and shaft of penis 2-3 minutes before intercourse or use as directed by a physician.
- Wash product off after intercourse.

Other Information

Store at 20-25° C (68-77° F)

Inactive Ingredients

Acrylates/C10-30 Alkyl Acrylate Crosspolymer, Diazolidinyl Urea, Ethoxydiglycol, Ginseng Root Extract, Methylparaben, Propanediol, Propylene Glycol, Propylparaben, Purified Water, Triethanolamine.

Distributed by Doc Johnson Enterprises.
P.O. Box 9908, North Hollywood, CA 91609-9908

PRINCIPAL DISPLAY PANEL - 56 g Tube Carton

ie
INTIMATE ENHANCEMENTS

PROLONGING™
with ginseng

MALE GENITAL
DESENSITIZING
DELAY CREAM

maximize performance
and partner satisfaction

Net Wt. 2oz. (56g)